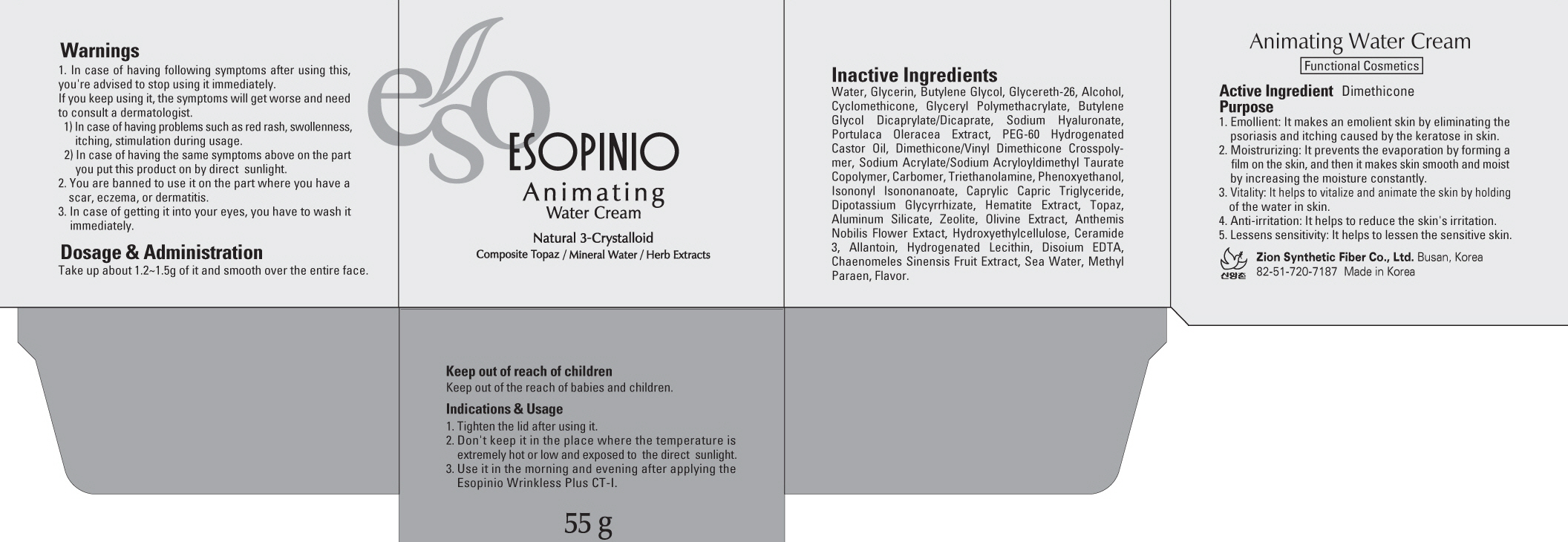 DRUG LABEL: ESOPINIO ANIMATING WATER
NDC: 44781-170 | Form: CREAM
Manufacturer: ZION SYNTHETIC FIBER CO., LTD.
Category: otc | Type: HUMAN OTC DRUG LABEL
Date: 20110829

ACTIVE INGREDIENTS: Dimethicone 0.55 g/55 g
INACTIVE INGREDIENTS: Water; GLYCERIN; Butylene Glycol; ALCOHOL; CYCLOMETHICONE; HYALURONATE SODIUM; POLYOXYL 60 HYDROGENATED CASTOR OIL; CARBOMER 934; TROLAMINE; Phenoxyethanol; MEDIUM-CHAIN TRIGLYCERIDES; ALUMINUM SILICATE; CHAMAEMELUM NOBILE; ALLANTOIN; EDETATE DISODIUM; METHYLPARABEN

Drug Facts

Active ingredient: DIMETHICONE

Inactive ingredients:
Water, Glycerin, Butylene Glycol, Glycereth-26, Alcohol, Cyclomethicone, Glyceryl, Polymethacrylate, Butylene Glycol Dicaprylate/Dicaprate, Sodium Hyaluronate, Portulaca Oleracea Extract, PEG-60 Hydrogenated Castor Oil, Dimethicone/Vinyl Dimethicone, Crosspolymer, Sodium Acrylate/Sodium Acryloyldimethyl Taurate Copolymer, Carbomer, Triethanolamine, Phenoxyethanol, Isononyl Isononanoate, Caprylic Capric Triglyceride, Dipotassium Glycyrrhizate, Hematite Extract, Topaz, Aluminum Silicate, Zeolite, Olivine Extract, Anthemis Nobilis Flower Extact, Hydroxyethylcellulose, Ceramide 3, Allantoin, Hydrogenated Lecithin, Disoium EDTA, Chaenomeles Sinensis Fruit Extract, Sea Water, Methyl Paraen, Flavor

Purpose:
It makes an emolient skin by eliminating the psoriasis and itching caused by the keratose in skin.
It prevents the evaporation by forming a film on the skin, and then it makes skin smooth and moist by increasing the moisture constantly.
It helps to vitalize and animate the skin by holding of the water in skin.
It helps to reduce the skin's irritation.
It helps to lessen the sensitive skin.

Warnings:
In case of having following symptoms after using this, you're advised to stop using it immediately. If you keep using it, the symptoms will get worse and need to consult a dermatologist.
- In case of having problems such as red rash, swollenness, itching, stimulation during usage.
- In case of having the same symptoms above on the part you put this product on by direct sunlight.
You are banned to use it on the part where you have a scar, eczema, or dermatitis.
In case of getting it into your eyes, you have to wash it immediately.

Keep out of reach of children:
Keep out of the reach of babies and children.

Indication and usage:
Tighten the lid after using it.
Don't keep it in the place where the temperature is extremely hot or low and exposed the direct sunlight.
Use it in the morning and evening after applying the Esopinio Wrinkless Plus CT-I.

Dosage and administration:
Take up about 1.2g - 1.5g of it and smooth over the entire face.